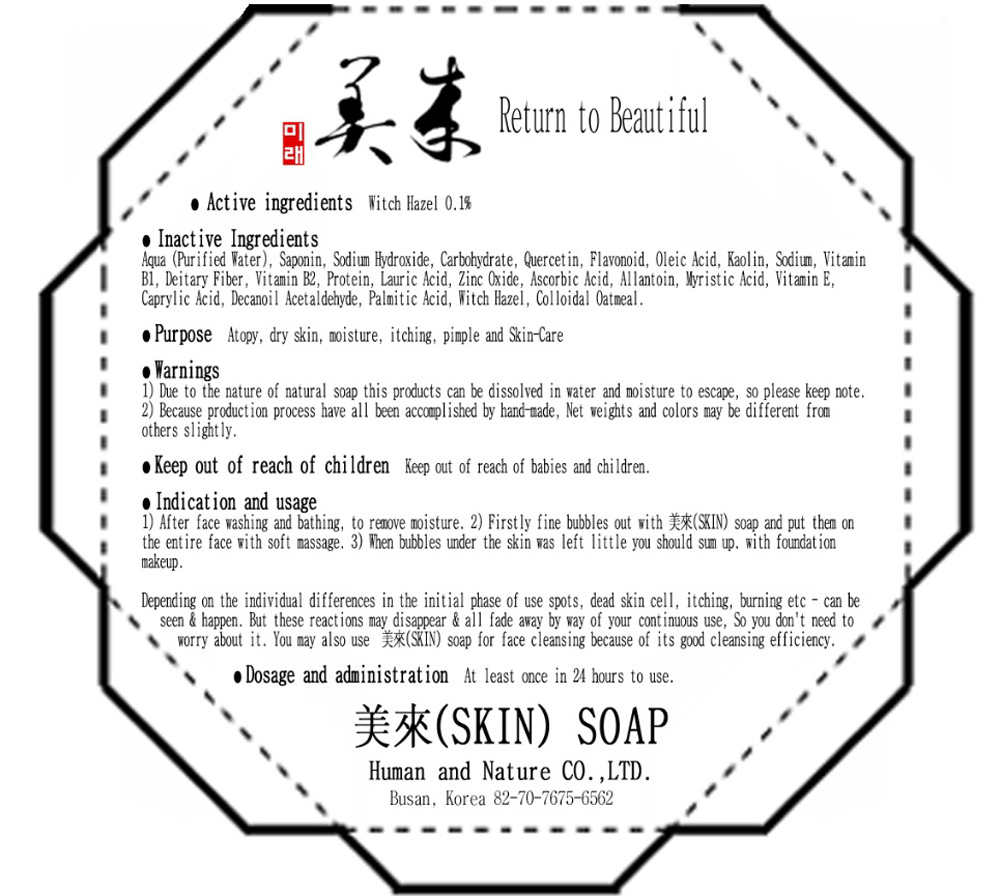 DRUG LABEL: MIRAE SKIN
NDC: 43071-100 | Form: SOAP
Manufacturer: HUMAN AND NATURE
Category: otc | Type: HUMAN OTC DRUG LABEL
Date: 20181219

ACTIVE INGREDIENTS: WITCH HAZEL 0.15 g/150 g
INACTIVE INGREDIENTS: WATER; KAOLIN

Drug Facts

Active Ingredient

Active ingredient: WITCH HAZEL 0.1%

Inactive Ingredients

Aqua (Purified Water), Saponin, Linoleic Acid, Sodium Hydroxide, Carbohydrate, Quercetin, Flavonoid, Oleic Acid, Kaolin, Sodium, Vitamin B1, dietary fiber, Vitamin B2, Protein, Lauric Acid, Zinc Oxide, Ascorbic Acid, Allantoin, Myristic Acid, Vitamin E, Caprylic Acid, Decanoil Acetaldehyde, Palmitic Acid, Colloidal Oatmeal

Purpose

Purpose: Atopy, Dry Skin, Moisture, Itching, Pimple and Skin-Care

Warnings

Due to the nature of natural soap this products can be dissolved in water and moisture to escape, so please keep note.
Because production process have all been accomplished by hand-made, Net weights and colors may be different from others slightly.

Keep out of reach of children

Keep out of reach of babies and children.

Uses

Indication and usage:
1. After face washing and bathing, to remove moisture.
2. Firstly fine bubbles out with SKIN soap and put them on the entire face with soft massage.
3. When bubbles under the skin was left little you should sum up with foundation makeup.

Directions

Dosage and administration:
At least once in 24 hours to use.